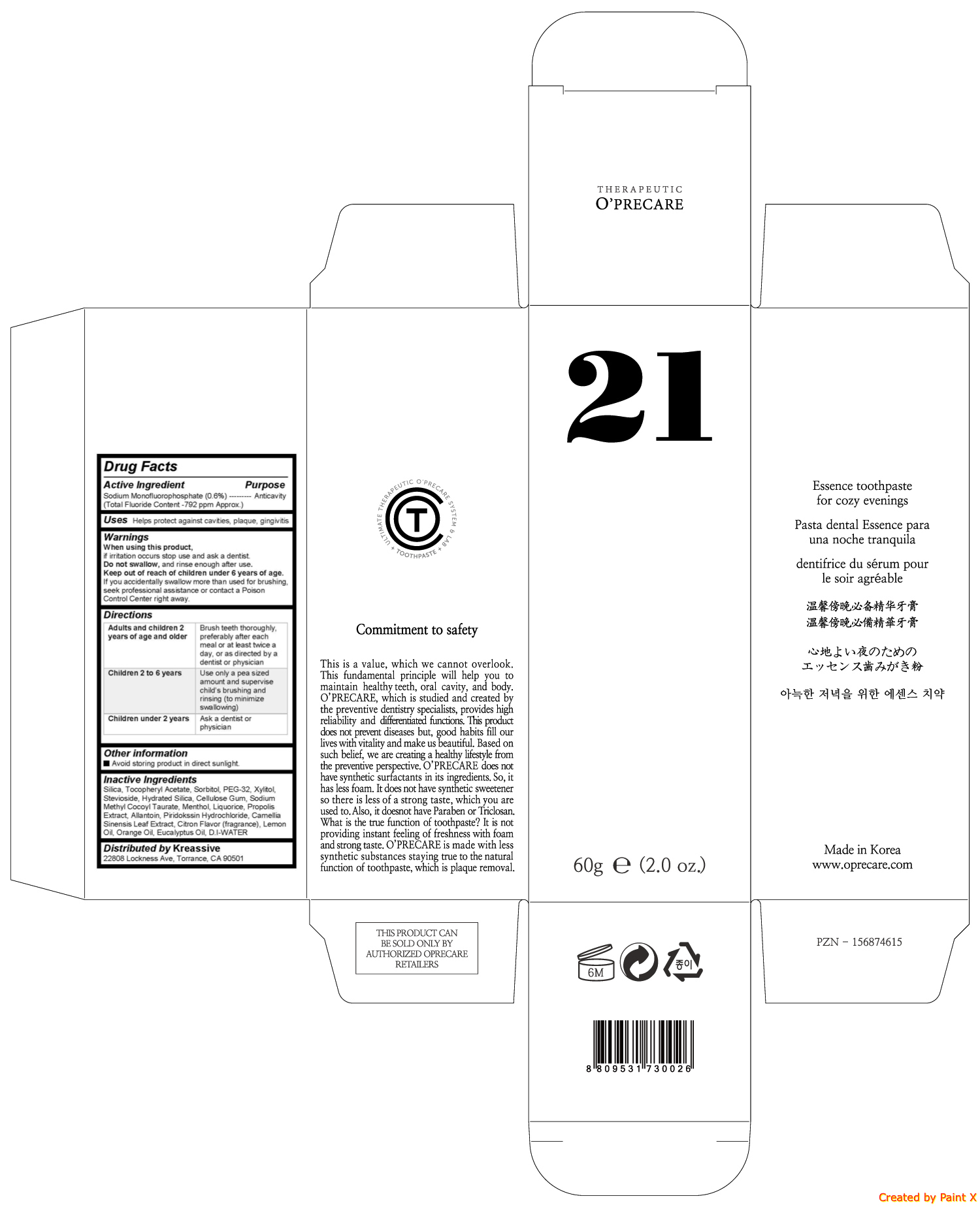 DRUG LABEL: OPRECARE 21
NDC: 71764-102 | Form: GEL
Manufacturer: O'PRECARE
Category: otc | Type: HUMAN OTC DRUG LABEL
Date: 20171012

ACTIVE INGREDIENTS: SODIUM MONOFLUOROPHOSPHATE 0.36 g/60 g
INACTIVE INGREDIENTS: SILICON DIOXIDE; .ALPHA.-TOCOPHEROL ACETATE; Sorbitol; POLYETHYLENE GLYCOL 1500; Xylitol; Stevioside; Hydrated Silica; CARBOXYMETHYLCELLULOSE SODIUM, UNSPECIFIED FORM; SODIUM METHYL COCOYL TAURATE; Menthol; LICORICE; PROPOLIS WAX; Allantoin; PIRIDOCAINE HYDROCHLORIDE; GREEN TEA LEAF; Lemon Oil; Orange Oil; Eucalyptus Oil

O'PRECARE 21

Active ingredient

Sodium Monofluorophosphate (0.6%)

Purpose

Anticavity

Warnings

When using this product, if irritation occurs stop use and ask a dentist. Do not swallow, and rinse enough after use. Keep out of reach of children under 6 years of age. If you accidentally swallow more than used for brushing, seek professional assistance or contact a Poison Control Center right away.

Uses

Helps protect against cavities, plaque, gingivitis

Directions

Adults and children 2 years of age and older | Brush teeth thoroughly, preferably after each meal or at least twice a day, or as directed by a dentist or physician
Children 2 to 6 years | Use only a pea sized amount and supervise childs brushing and rinsing (to minimize swallowing)
Children under 2 years | Ask a dentist or physician

Keep out of reach of children under 6 years of age. If you accidentally swallow more than used for brushing, seek professional assistance or contact a Poison Control Center right away.

Inactive ingredients

Silica, Tocopheryl Acetate, Piridokssin Hydrochloride, Sodium Pyrophosphate, Sorbitol, PEG-32, Hydrated Silica, Cellulose Gum, Titanium Oxide, Xylitol, Stevioside, Camellia Sinensis Leaf Extract, Sodium Methyl Cocoyl Taurate, Ubidecarenone, Cnidium Extract, Menthol, Mint Flavor (Fragrance), Chamomilla Recutita (Matricaria) Flower Extract, Peppermint Flavor (fragrance), D.I-WATER